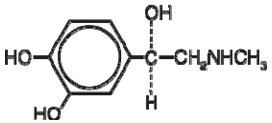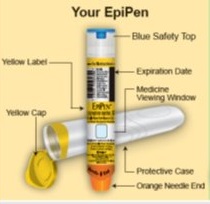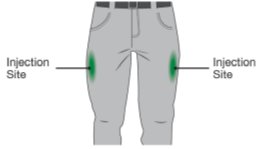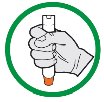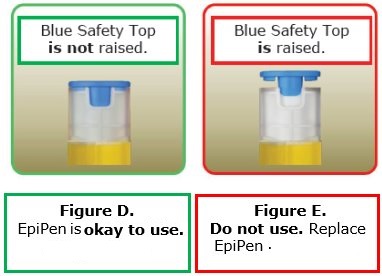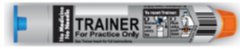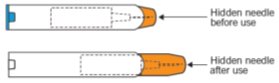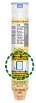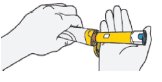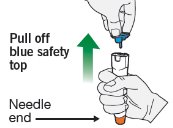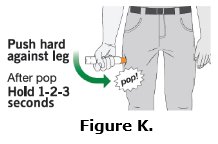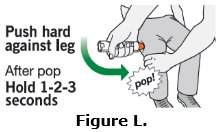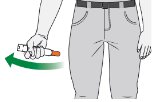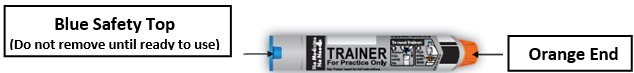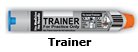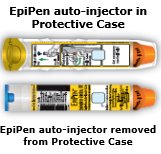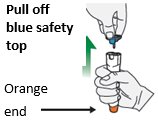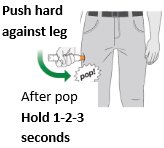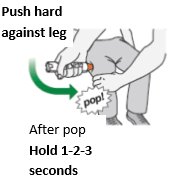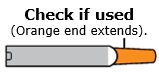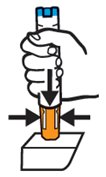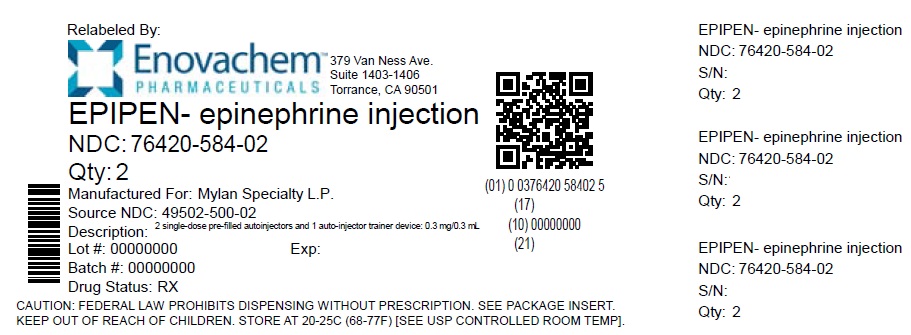 DRUG LABEL: EPIPEN
NDC: 76420-584 | Form: INJECTION
Manufacturer: Asclemed USA, Inc.
Category: prescription | Type: HUMAN PRESCRIPTION DRUG LABEL
Date: 20230829

ACTIVE INGREDIENTS: EPINEPHRINE 0.3 mg/0.3 mL
INACTIVE INGREDIENTS: SODIUM CHLORIDE; SODIUM METABISULFITE; HYDROCHLORIC ACID; WATER

HIGHLIGHTS OF PRESCRIBING INFORMATION

These highlights do not include all the information needed to use EPIPEN®safely and effectively. See full prescribing information for EPIPEN.
EPIPEN®(epinephrine injection), for intramuscular or subcutaneous use
Initial U.S. Approval: 1939

1 INDICATIONS AND USAGE

EpiPen are non-selective alpha and beta-adrenergic receptor agonist indicated in the emergency treatment of allergic reactions (Type I) including anaphylaxis. (1)

2 DOSAGE AND ADMINISTRATION

- Patients greater than or equal to 30 kg (66 lbs): EpiPen 0.3 mg (2)

Inject intramuscularly or subcutaneously into the anterolateral aspect of the thigh, through clothing if necessary. Each device is a single-dose injection .(2)

3 DOSAGE FORMS AND STRENGTHS

- Injection: 0.3 mg (0.3 mg/0.3 mL) single-dose pre-filled auto-injector (3)

4 CONTRAINDICATIONS

None (4)

5 WARNINGS AND PRECAUTIONS

- In conjunction with use, seek immediate medical or hospital care. (5.1)
- Do not inject intravenously, into buttock, or into digits, hands, or feet. (5.2)
- To minimize the risk of injection related injury, hold the child’s leg firmly in place and limit movement prior to and during injection when administering to young children. (5.2)
- Rare cases of serious skin and soft tissue infections have been reported following epinephrine injection. Advise patients to seek medical care if they develop signs or symptoms of infection. (5.3)
- The presence of a sulfite in this product should not deter use. (5.4)
- Administer with caution in patients with heart disease; may aggravate angina pectoris or produce ventricular arrhythmias. (5.5)

6 ADVERSE REACTIONS

Adverse reactions to epinephrine include anxiety, apprehensiveness, restlessness, tremor, weakness, dizziness, sweating, palpitations, pallor, nausea and vomiting, headache, and/or respiratory difficulties. (6)

To report SUSPECTED ADVERSE REACTIONS, contact Mylan at 1-877-446-3679 (1-877-4-INFO-RX) or FDA at 1-800-FDA-1088 or www.fda.gov/medwatch.

7 DRUG INTERACTIONS

- Cardiac glycosides or diuretics: observe for development of cardiac arrhythmias. (7)
- Tricyclic antidepressants, monoamine oxidase inhibitors, levothyroxine sodium, and certain antihistamines potentiate effects of epinephrine. (7)
- Beta-adrenergic blocking drugs antagonize cardiostimulating and bronchodilating effects of epinephrine. (7)
- Alpha-adrenergic blocking drugs antagonize vasoconstricting and hypertensive effects of epinephrine. (7)
- Ergot alkaloids may reverse the pressor effects of epinephrine. (7)

8 USE IN SPECIFIC POPULATIONS

- Elderly patients may be at greater risk of developing adverse reactions. (5.5, 8.5)

FULL PRESCRIBING INFORMATION

1 INDICATIONS AND USAGE

EpiPen are indicated in the emergency treatment of allergic reactions (Type I) including anaphylaxis to stinging insects (e.g., order Hymenoptera, which include bees, wasps, hornets, yellow jackets and fire ants) and biting insects (e.g., triatoma, mosquitoes), allergen immunotherapy, foods, drugs, diagnostic testing substances (e.g., radiocontrast media) and other allergens, as well as idiopathic anaphylaxis or exercise-induced anaphylaxis. EpiPen are intended for immediate administration in patients who are determined to be at increased risk for anaphylaxis, including individuals with a history of anaphylactic reactions. Anaphylactic reactions may occur within minutes after exposure and consist of flushing, apprehension, syncope, tachycardia, thready or unobtainable pulse associated with a fall in blood pressure, convulsions, vomiting, diarrhea and abdominal cramps, involuntary voiding, wheezing, dyspnea due to laryngeal spasm, pruritus, rashes, urticaria or angioedema. EpiPen are intended for immediate administration as emergency supportive therapy only and are not a substitute for immediate medical care.

2 DOSAGE AND ADMINISTRATION

2.1 Recommended Dosage According to Patient Body Weight

- Patients greater than or equal to 30 kg (approximately 66 pounds or more): EpiPen 0.3 mg

2.2 Administration Instructions

- Inject the single-dose EpiPen intramuscularly or subcutaneously into the anterolateral aspect of the thigh, through clothing if necessary. Do not inject intravenously, and do not inject into buttocks, into digits, hands or feet [see Warnings and Precautions (5.2)].
- Instruct caregivers of young children who are prescribed an EpiPen and who may be uncooperative and kick or move during an injection to hold the leg firmly in place and limit movement prior to and during an injection [see Warnings and Precautions (5.2)] .
- Each EpiPen is a single-dose epinephrine injection for single use. Since the doses of epinephrine delivered from EpiPen are fixed, consider using other forms of injectable epinephrine if doses lower than 0.15 mg are deemed necessary.
- With severe persistent anaphylaxis, repeat injections with an additional EpiPen may be necessary. More than two sequential doses of epinephrine should only be administered under direct medical supervision [see Warnings and Precautions (5.1)] .
- The epinephrine solution in the clear window of the EpiPen Auto-Injector should be inspected visually for particulate matter and discoloration.

Discarding After Use:

The EpiPen each contain 2 mL epinephrine solution. Approximately 1.7 mL remains in the auto-injector after activation, but is not available for future use, and should be discarded .

3 DOSAGE FORMS AND STRENGTHS

- Injection: 0.3 mg (0.3 mg/0.3 mL), clear and colorless solution in single-dose pre-filled auto-injector

4 CONTRAINDICATIONS

None

5 WARNINGS AND PRECAUTIONS

5.1 Emergency Treatment

EpiPen are intended for immediate administration as emergency supportive therapy and are not intended as a substitute for immediate medical care. In conjunction with the administration of epinephrine, the patient should seek immediate medical or hospital care. More than two sequential doses of epinephrine should only be administered under direct medical supervision [ see Indications and Usage (1), Dosage and Administration (2)and Patient Counseling Information (17)].

5.2 Injection-Related Complications

EpiPen should onlybe injected into the anterolateral aspect of the thigh [ see Dosage and Administration (2)and Patient Counseling Information (17)].

Do not inject intravenously

Large doses or accidental intravenous injection of epinephrine may result in cerebral hemorrhage due to sharp rise in blood pressure. Rapidly acting vasodilators can counteract the marked pressor effects of epinephrine if there is such inadvertent administration.

Do not inject into buttock

Injection into the buttock may not provide effective treatment of anaphylaxis. Advise the patient to go immediately to the nearest emergency room for further treatment of anaphylaxis. Additionally, injection into the buttock has been associated with Clostridial infections (gas gangrene). Cleansing with alcohol does not kill bacterial spores, and therefore, does not lower this risk.

Do not inject into digits, hands or feet

Since epinephrine is a strong vasoconstrictor, accidental injection into the digits, hands or feet may result in loss of blood flow to the affected area. Advise the patient to go immediately to the nearest emergency room and to inform the healthcare provider in the emergency room of the location of the accidental injection. Treatment of such inadvertent administration should consist of vasodilation, in addition to further appropriate treatment of anaphylaxis [ see Adverse Reactions (6)].

Hold leg firmly during injection

Lacerations, bent needles, and embedded needles have been reported when EpiPen have been injected into the thigh of young children who are uncooperative and kick or move during an injection. To minimize the risk of injection related injury when administering, hold the child’s leg firmly in place and limit movement prior to and during injection.

5.3 Serious Infections at the Injection Site

Rare cases of serious skin and soft tissue infections, including necrotizing fasciitis and myonecrosis caused by Clostridia (gas gangrene), have been reported at the injection site following epinephrine injection for anaphylaxis. Clostridiumspores can be present on the skin and introduced into the deep tissue with subcutaneous or intramuscular injection. While cleansing with alcohol may reduce presence of bacteria on the skin, alcohol cleansing does not kill Clostridiumspores. To decrease the risk of Clostridiuminfection, do not inject EpiPen into the buttock [see Warnings and Precautions (5.2)]. Advise patients to seek medical care if they develop signs or symptoms of infection, such as persistent redness, warmth, swelling, or tenderness, at the epinephrine injection site.

5.4 Allergic Reactions Associated with Sulfite

The presence of a sulfite in this product should not deter administration of the drug for treatment of serious allergic or other emergency situations even if the patient is sulfite-sensitive.

Epinephrine is the preferred treatment for serious allergic reactions or other emergency situations even though this product contains sodium metabisulfite, a sulfite that may, in other products, cause allergic-type reactions including anaphylactic symptoms or life-threatening or less severe asthmatic episodes in certain susceptible persons.

The alternatives to using epinephrine in a life-threatening situation may not be satisfactory.

5.5 Disease Interactions

Some patients may be at greater risk for developing adverse reactions after epinephrine administration. Despite these concerns, it should be recognized that the presence of these conditions is not a contraindication to epinephrine administration in an acute, life-threatening situation. Therefore, patients with these conditions, and/or any other person who might be in a position to administer EpiPen to a patient experiencing anaphylaxis should be carefully instructed in regard to the circumstances under which epinephrine should be used.

Patients with Heart Disease

Epinephrine should be administered with caution to patients who have heart disease, including patients with cardiac arrhythmias, coronary artery or organic heart disease, or hypertension .In such patients, or in patients who are on drugs that may sensitize the heart to arrhythmias ,epinephrine may precipitate or aggravate angina pectoris as well as produce ventricular arrhythmias [ see Drug Interactions (7)and Adverse Reactions (6)].

Other Patients and Diseases

Epinephrine should be administered with caution to patients with hyperthyroidism, diabetes, elderly individuals, and pregnant women. Patients with Parkinson’s disease may notice a temporary worsening of symptoms.

6 ADVERSE REACTIONS

Due to the lack of randomized, controlled clinical trials of epinephrine for the treatment of anaphylaxis, the true incidence of adverse reactions associated with the systemic use of epinephrine is difficult to determine. Adverse reactions reported in observational trials, case reports, and studies are listed below.

Common adverse reactions to systemically administered epinephrine include anxiety; apprehensiveness; restlessness; tremor; weakness; dizziness; sweating; palpitations; pallor; nausea and vomiting; headache; and/or respiratory difficulties. These symptoms occur in some persons receiving therapeutic doses of epinephrine, but are more likely to occur in patients with hypertension or hyperthyroidism [ see Warnings and Precautions (5.5)].

Cardiovascular Reactions

- Arrhythmias, including fatal ventricular fibrillation, have been reported, particularly in patients with underlying cardiac disease or those receiving certain drugs [ see Warnings and Precautions (5.5)and Drug Interactions (7)].
- Rapid rises in blood pressure have produced cerebral hemorrhage, particularly in elderly patients with cardiovascular disease [ see Warnings and Precautions (5.5)].
- Angina may occur in patients with coronary artery disease [ see Warnings and Precautions (5.5)].
- Rare cases of stress cardiomyopathy have been reported in patients treated with epinephrine.

Reactions from Accidental Injection and/or Improper Technique

- Accidental injection into the digits, hands or feet may result in loss of blood flow to the affected area [ see Warnings and Precautions (5.2)].
- Adverse reactions experienced as a result of accidental injections may include increased heart rate, local reactions including injection site pallor, coldness and hypoesthesia or injury at the injection site resulting in bruising, bleeding, discoloration, erythema or skeletal injury.
- Lacerations, bent needles, and embedded needles have been reported when EpiPen has been injected into the thigh of young children who are uncooperative and kick or move during the injection [ see Warning and Precautions (5.2)].
- Injection into the buttock has resulted in cases of gas gangrene [ see Warnings and Precautions (5.2)] .

Skin and Soft Tissue Infections

- Rare cases of serious skin and soft tissue infections, including necrotizing fasciitis and myonecrosis caused by Clostridia (gas gangrene), have been reported following epinephrine injection, including EpiPen, in the thigh [ see Warnings and Precautions (5.3)].

7 DRUG INTERACTIONS

Cardiac Glycosides, Diuretics, and Anti-arrhythmics

Patients who receive epinephrine while concomitantly taking cardiac glycosides, diuretics, or anti-arrhythmics should be observed carefully for the development of cardiac arrhythmias [see Warnings and Precautions (5.5)] .

Antidepressants, Monoamine Oxidase Inhibitors, Levothyroxine, and Antihistamines

The effects of epinephrine may be potentiated by tricyclic antidepressants, monoamine oxidase inhibitors, levothyroxine sodium, and certain antihistamines, notably chlorpheniramine, tripelennamine, and diphenhydramine.

Beta-Adrenergic Blockers

The cardiostimulating and bronchodilating effects of epinephrine are antagonized by beta- adrenergic blocking drugs, such as propranolol.

Alpha-Adrenergic Blockers

The vasoconstricting and hypertensive effects of epinephrine are antagonized by alpha- adrenergic blocking drugs, such as phentolamine.

Ergot Alkaloids

Ergot alkaloids may also reverse the pressor effects of epinephrine.

8 USE IN SPECIFIC POPULATIONS

8.1 Pregnancy

Risk Summary

There are no adequate and well controlled studies of the acute effect of epinephrine in pregnant women. In animal reproductive studies, epinephrine administered by the subcutaneous route to rabbits, mice, and hamsters during the period of organogenesis was teratogenic at doses 7 times and higher than the maximum recommended human intramuscular and subcutaneous dose on a mg/m^2basis. Epinephrine is the first-line medication of choice for the treatment of anaphylaxis during pregnancy in humans. Epinephrine should be used for treatment of anaphylaxis during pregnancy in the same manner as it is used in non-pregnant patients.

In the U.S. general population, the estimated background risk of major birth defects and miscarriage in clinically recognized pregnancies is 2 to 4% and 15 to 20%, respectively.

Clinical Considerations

Disease-associated maternal and embryo/fetal risk

During pregnancy, anaphylaxis can be catastrophic and can lead to hypoxic-ischemic encephalopathy and permanent central nervous system damage or death in the mother and, more commonly, in the fetus or neonate. The prevalence of anaphylaxis occurring during pregnancy is reported to be approximately 3 cases per 100,000 deliveries.

Management of anaphylaxis during pregnancy is similar to management in the general population. Epinephrine is the first line-medication of choice for treatment of anaphylaxis; it should be used in the same manner in pregnant and non-pregnant patients. In conjunction with the administration of epinephrine, the patient should seek immediate medical or hospital care.

Data

Animal Data

In an embryofetal development study with rabbits dosed during the period of organogenesis, epinephrine was shown to be teratogenic (including gastroschisis and embryonic lethality) at doses approximately 40 times the maximum recommended intramuscular or subcutaneous dose (on a mg/m^2basis at a maternal subcutaneous dose of 1.2 mg/kg/day for two to three days).

In an embryofetal development study with mice dosed during the period of organogenesis, epinephrine was shown to be teratogenic (including embryonic lethality) at doses approximately 8 times the maximum recommended intramuscular or subcutaneous dose (on a mg/m^2basis at maternal subcutaneous dose of 1 mg/kg/day for 10 days). These effects were not seen in mice at approximately 4 times the maximum recommended daily intramuscular or subcutaneous dose (on a mg/m^2basis at a subcutaneous maternal dose of 0.5 mg/kg/day for 10 days).

In an embryofetal development study with hamsters dosed during the period of organogenesis from gestation days 7 to 10, epinephrine was shown to be teratogenic at doses approximately 7 times the maximum recommended intramuscular or subcutaneous dose (on a mg/m^2basis at a maternal subcutaneous dose of 0.5 mg/kg/day).

8.2 Lactation

Risk Summary

There is no information on the presence of epinephrine in human milk, the effects on breastfed infants, or the effects on milk production. Epinephrine is the first line-medication of choice for treatment of anaphylaxis; it should be used in the same manner in breastfeeding and non-breastfeeding patients.

8.4 Pediatric Use

EpiPen may be administered to pediatric patients at a dosage appropriate to body weight [ see Dosage and Administration (2.1)] .Clinical experience with the use of epinephrine suggests that the adverse reactions seen in children are similar in nature and extent to those both expected and reported in adults. Since the doses of epinephrine delivered from EpiPen are fixed, consider using other forms of injectable epinephrine if doses lower than 0.15 mg are deemed necessary.

8.5 Geriatric Use

Clinical studies for the treatment of anaphylaxis have not been performed in subjects aged 65 and over to determine whether they respond differently from younger subjects. However, other reported clinical experience with use of epinephrine for the treatment of anaphylaxis has identified that geriatric patients may be particularly sensitive to the effects of epinephrine. Therefore, EpiPen should be administered with caution in elderly individuals, who may be at greater risk for developing adverse reactions after epinephrine administration [ see Warnings and Precautions (5.5), Overdosage (10)].

10 OVERDOSAGE

Overdosage of epinephrine may produce extremely elevated arterial pressure, which may result in cerebrovascular hemorrhage, particularly in elderly patients. Overdosage may also result in pulmonary edema because of peripheral vascular constriction together with cardiac stimulation. Treatment consists of rapidly acting vasodilators or alpha-adrenergic blocking drugs and/or respiratory support.

Epinephrine overdosage can also cause transient bradycardia followed by tachycardia, and these may be accompanied by potentially fatal cardiac arrhythmias. Premature ventricular contractions may appear within one minute after injection and may be followed by multifocal ventricular tachycardia (prefibrillation rhythm). Subsidence of the ventricular effects may be followed by atrial tachycardia and occasionally by atrioventricular block. Treatment of arrhythmias consists of administration of a beta-adrenergic blocking drug such as propranolol.

Overdosage sometimes results in extreme pallor and coldness of the skin, metabolic acidosis, and kidney failure. Suitable corrective measures must be taken in such situations.

11 DESCRIPTION

EpiPen (epinephrine injection, USP) 0.3 mg are single-dose auto-injectors and combination products containing drug and device components.

Each EpiPen Auto-Injector, 0.3 mg delivers a single dose of 0.3 mg epinephrine from epinephrine injection, USP 0.3 mg/0.3 mL in a sterile solution.

Each 0.3 mL in the EpiPen Auto-Injector contains 0.3 mg epinephrine, 1.8 mg sodium chloride, 0.5 mg sodium metabisulfite, hydrochloric acid to adjust pH, and Water for Injection. The pH range is 2.2-5.0.

Epinephrine is a sympathomimetic catecholamine. Chemically, epinephrine is (-)-3,4- Dihydroxy-α-[(methylamino)methyl]benzyl alcohol with the following structure:

Epinephrine solution deteriorates rapidly on exposure to air or light, turning pink from oxidation to adrenochrome and brown from the formation of melanin. Replace EpiPen if the epinephrine solution appears discolored (pinkish or brown color), cloudy, or contains particles.

Thoroughly review the patient instructions and operation of EpiPen with patients and caregivers prior to use [ see Patient Counseling Information (17)].

12 CLINICAL PHARMACOLOGY

12.1 Mechanism of Action

Epinephrine acts on both alpha- and beta-adrenergic receptors.

12.2 Pharmacodynamics

Through its action on alpha-adrenergic receptors, epinephrine lessens the vasodilation and increased vascular permeability that occurs during anaphylaxis, which can lead to loss of intravascular fluid volume and hypotension.

Through its action on beta-adrenergic receptors, epinephrine causes bronchial smooth muscle relaxation and helps alleviate bronchospasm, wheezing and dyspnea that may occur during anaphylaxis.

Epinephrine also alleviates pruritus, urticaria, and angioedema and may relieve gastrointestinal and genitourinary symptoms associated with anaphylaxis because of its relaxer effects on the smooth muscle of the stomach, intestine, uterus and urinary bladder.

When given subcutaneously or intramuscularly, epinephrine has a rapid onset and short duration of action.

13 NONCLINICAL TOXICOLOGY

13.1 Carcinogenesis, Mutagenesis, Impairment of Fertility

Long-term studies to evaluate the carcinogenic potential of epinephrine have not been conducted.

Epinephrine and other catecholamines have been shown to have mutagenic potential in vitro. Epinephrine was positive in the Salmonellabacterial reverse mutation assay, positive in the mouse lymphoma assay, and negative in the in vivomicronucleus assay. Epinephrine is an oxidative mutagen based on the E. coliWP2 Mutoxitest bacterial reverse mutation assay. This should not prevent the use of epinephrine where indicated [see Indications and Usage (1)].

The potential for epinephrine to impair reproductive performance has not been evaluated, but epinephrine has been shown to decrease implantation in female rabbits dosed subcutaneously with 1.2 mg/kg/day (40-fold the highest human intramuscular or subcutaneous daily dose) during gestation days 3 to 9.

16 HOW SUPPLIED/STORAGE AND HANDLING

How Supplied

- EpiPen 2-Pak (epinephrine) injection is supplied with 2 single-dose pre-filled auto-injectors and 1 auto-injector trainer device: 0.3 mg/0.3 mL (NDC 76420-584-02 relabeled from NDC 49502-500-02)

EpiPen 2-Pak®also include an S-clip to clip two carrier tubes together.

Storage and Handling

- Protect from light. Epinephrine is light sensitive and should be stored in the carrier tube provided to protect it from light.
- Store at 20°C to 25°C (68°F to 77°F); excursions permitted to 15°C to 30°C (59°F to 86°F) [See USP Controlled Room Temperature].
- Do not refrigerate.
- Before using, check to make sure the solution in the auto-injector is clear and colorless.
- Replace the auto-injector if the solution is discolored (pinkish or brown color), cloudy, or contains particle.
- Properly dispose all used, unwanted or expired EpiPen auto-injectors.

17 PATIENT COUNSELING INFORMATION

See FDA-Approved Patient Labeling (Patient Information and Instructions for Use)

A healthcare provider should review the patient instructions and operation of EpiPen in detail, with the patient or caregiver.

Epinephrine is essential for the treatment of anaphylaxis. Patients who are at risk of or with a history of severe allergic reactions (anaphylaxis) to insect stings or bites, foods, drugs, and other allergens, as well as idiopathic and exercise-induced anaphylaxis, should be carefully instructed about the circumstances under which epinephrine should be used.

Administration

Instruct patients and/or caregivers in the appropriate use of EpiPen. EpiPen should be injected into the middle of the outer thigh (through clothing, if necessary). Each device is a single-use injection. Advise patients to seek immediate medical care in conjunction with administration of EpiPen.

Instruct caregivers to hold the leg of young children firmly in place and limit movement prior to and during injection. Lacerations, bent needles, and embedded needles have been reported when EpiPen have been injected into the thigh of young children who are uncooperative and kick or move during an injection [ see Warnings and Precautions (5.2)].

Instruct patients and/or caregivers to throw away the blue safety release immediately after using EpiPen. This small part may pose a choking hazard for children.

Complete patient information, including dosage, directions for proper administration and precautions can be found inside each EpiPen carton. A printed label on the surface of EpiPen shows instructions for use and a diagram depicting the injection process.

Training

Instruct patients and/or caregivers to use and practice with the Trainer to familiarize themselves with the use of EpiPen in an allergic emergency. The Trainer may be used multiple times. A Trainer device is provided in 2-Pak cartons.

Instruct patients and/or caregivers to immediately place the blue safety release back on the Trainer and reset it after practicing. This small part may pose a choking hazard for children.

Adverse Reactions

Epinephrine may produce symptoms and signs that include an increase in heart rate, the sensation of a more forceful heartbeat, palpitations, sweating, nausea and vomiting, difficulty breathing, pallor, dizziness, weakness or shakiness, headache, apprehension, nervousness, or anxiety. These signs and symptoms usually subside rapidly, especially with rest, quiet and recumbency. Patients with hypertension or hyperthyroidism may develop more severe or persistent effects, and patients with coronary artery disease could experience angina. Patients with diabetes may develop increased blood glucose levels following epinephrine administration. Patients with Parkinson’s disease may notice a temporary worsening of symptoms [ see Warnings and Precautions (5.5)] .

Accidental Injection

Advise patients to seek immediate medical care in the case of accidental injection. Since epinephrine is a strong vasoconstrictor when injected into the digits, hands, or feet, treatment should be directed at vasodilatation if there is such an accidental injection to these areas [ see Warnings and Precautions (5.2)].

Serious Infections at the Injection Site

Rare cases of serious skin and soft tissue infections, including necrotizing fasciitis and myonecrosis caused by Clostridia (gas gangrene), have been reported at the injection site following epinephrine injection for anaphylaxis. Advise patients to seek medical care if they develop signs or symptoms of infection, such as persistent redness, warmth, swelling, or tenderness, at the epinephrine injection site [ see Warnings and Precautions (5.3)].

Storage and Handling

Instruct patients to inspect the epinephrine solution visually through the clear window of the auto-injector periodically. Replace EpiPen if the epinephrine solution appears discolored (pinkish or brown color), cloudy, or contains particles. Epinephrine is light sensitive and should be stored in the carrier tube provided to protect it from light. The carrier tube is not waterproof. Instruct patients that EpiPen must be used or properly disposed once the blue safety release is removed or after use [ see Storage and Handling (16.2)].

Advise patients and caregivers to give used EpiPen auto-injectors to their healthcare provider for inspection and proper disposal.

Advise patients and caregivers to promptly dispose of medicines that are no longer needed. Dispose of expired, unwanted, or unused EpiPen auto-injectors in an FDA-cleared sharps container. Instruct patients not to dispose EpiPen in their household trash. Instruct patients that if they do not have a FDA-cleared sharps disposal container, they may use a household container that is made of a heavy-duty plastic, can be closed with a tight-fitting and puncture-resistant lid without sharps being able to come out, upright and stable during use, leak-resistant, and properly labeled to warn of hazardous waste inside the container. Inform patients that they can visit the FDA website for additional information on disposal of unused medicines.

Complete patient information, including dosage, directions for proper administration and precautions can be found inside each EpiPen Auto-Injector carton.

Relabeled by:

Enovachem PHARMACEUTICALS

Torrance, CA 90501

PATIENT INFORMATION and INSTRUCTIONS FOR USE

EPIPEN®[/epeepen/]
(epinephrine injection, USP) Auto-Injector 0.3 mg
EpiPen®= one dose of 0.3 mg epinephrine, USP 0.3 mg/0.3 mL

For allergic emergencies (anaphylaxis)

PATIENT INFORMATION

Read this Patient Information leaflet carefully before using the EpiPen®auto-injector and each time you get a refill. There may be new information. Anyone who may be able to administer the EpiPen auto-injector should know how to use it before you have an allergic emergency.

This information does not take the place of talking with your healthcare provider about your medical condition or your treatment.

What is the most important information I should know about EpiPen?

1. EpiPen are single-dose automatic injection devices (auto-injectors) that contain epinephrine. Epinephrine is a medicine used to treat allergic emergencies (anaphylaxis). Anaphylaxis can be life threatening and can happen within minutes. If untreated, anaphylaxis can lead to death. This allergic emergency can be caused by stinging and biting insects, allergy injections, foods, medicines, exercise, or unknown causes.

Symptoms of anaphylaxis may include:

- trouble breathing
- wheezing
- hoarseness (changes in the way your voice sounds)
- hives (raised reddened rash that may itch)
- severe itching
- swelling of your face, lips, mouth, or tongue
- skin rash, redness, or swelling
- fast heartbeat
- weak pulse
- feeling very anxious
- confusion
- stomach pain
- losing control of urine or bowel movements (incontinence)
- diarrhea or stomach cramps
- dizziness, fainting, or “passing out” (unconsciousness)

2. Always carry 2 EpiPen auto-injectorswith you because sometimes a single dose of epinephrine may not be enough to treat a serious allergic reaction before seeking medical care. You also need to always carry 2 auto-injectors with you if the first auto-injector is activated before the dose can be given. A device that has been activated by accident cannot be used in an allergic emergency (anaphylaxis).

Note: The EpiPen auto-injector has been activated when the blue safety top is removed and a “pop” is heard, the orange needle end of the auto-injector is extended, or the medicine viewing window is blocked.
You may not know when anaphylaxis will happen. Talk to your healthcare provider if you need more auto-injectors to keep at work, school, or other locations. If you use 1 EpiPen 1 to treat an emergency allergic reaction, be sure to replace it so you always carry 2 auto-injectors. Tell your family members, caregivers, and others where you keep your EpiPen auto-injectors. Make sure they know how to use it before you need it. You may be unable to speak in an allergic emergency.

3. When you have an allergic emergency (anaphylaxis) use your EpiPen auto-injector right away.Get emergency medical help right away even if you have used the EpiPen auto-injector. You can use a second EpiPen auto-injector if symptoms continue or come back or if the first auto-injector is activated before the dose can be given. For this reason, you should carry 2 EpiPen auto-injectors with you at all times. If you need more than 2 doses for an allergic emergency, they must be given by a healthcare provider.

What are EpiPen auto-injectors?

- EpiPen auto-injectors are disposable, prefilled auto-injectors used to treat life-threatening, allergic emergencies in people who are at risk for or have a history of serious allergic emergencies. Each device contains one dose of epinephrine.
- EpiPen auto-injectors are for immediate administration by you or your caregiver. They do not take the place of emergency medical care. You should get emergency help right away after using your EpiPen auto-injector.
- EpiPen auto-injectors are for people who have been prescribed this medicine by their healthcare provider.
- The EpiPen (0.3 mg) auto-injector is for people who weigh 66 pounds or more (30 kilograms or more).
- It is not known if EpiPen are safe and effective in children who weigh less than 33 pounds (15 kilograms).

What should I tell my healthcare provider before using EpiPen ?

Before you use your EpiPen auto-injector, tell your healthcare provider about all your medical conditions. Your healthcare provider may give you more instructions about when and how to use EpiPen if you have the following:

- heart problems or high blood pressure
- diabetes
- thyroid problems
- asthma
- a history of depression
- Parkinson’s disease

You may also receive more instructions if you:

- are pregnant or plan to become pregnant. It is not known if epinephrine will harm your unborn baby.
- are breastfeeding or plan to breastfeed. It is not known if epinephrine passes into your breast milk.

Tell your healthcare provider about all the medicines you take, including prescription and over-the-counter medicines, vitamins and herbal supplements. Tell your healthcare provider about all of your known allergies.

Especially tell your healthcare provider if you take certain asthma medicines.

EpiPen other medicines may affect each other, causing side effects. EpiPen may affect the way other medicines work. Other medicines may affect how EpiPen works.

Know the medicines you take. Keep a list of all your medicines, including over-the-counter medicines, vitamins and herbal supplements to show your healthcare provider and pharmacist when you get a new medicine.

Use your EpiPen auto-injector for treatment of anaphylaxis as prescribed by your healthcare provider, regardless of your medical conditions or the medicines you take.

How should I use the EpiPen auto-injector?

- Use your single-dose EpiPen auto-injector exactly as your healthcare provider tells you to use it. You may need to use a second EpiPen auto-injector if symptoms continue or come back while you wait for emergency help or if the first auto-injector is activated before the dose can be given. If you need more than 2 doses of epinephrine for a single anaphylaxis episode, more doses must be administered by a healthcare provider.
- EpiPen should be injected into the middle of your outer thigh (upper leg). It can be injected through your clothing if needed. Do notinject into a vein or into the buttocks, fingers, toes, hands or feet.
- Read and make sure you understand the Instructions for Use at the end of this Patient Information leaflet to learn the right way to use the EpiPen auto-injector.
- Your healthcare provider will show you how to safely use the EpiPen auto-injector.
- It is very important that you hold the EpiPen auto-injector down firmly on the middle of the outer thigh (upper leg) for at least 3 full seconds. If you do not hold it in place long enough, the EpiPen auto-injector might not have time to deliver the correct dose of medicine.• Caution: Never put your thumb, fingers or hand over the orange needle end. Never press or push the orange needle end with your thumb, fingers or hand. The needle comes out of the orange needle end. Accidental injection into fingers, hands or feet may cause a loss of blood flow to these areas. If an accidental injection happens, go immediately to the nearest emergency room.
- Warning: Do notflip the blue safety top off using a thumb or by pulling it sideways, or by bending and twisting the blue safety top. This may cause the device to activate by accident: a “pop” is heard, the orange needle end is extended and the medicine viewing window is blocked. A device that has been activated by accident cannot be used in an emergency.If this happens, replace it with a new EpiPen .
- When you are ready to inject, pull the blue safety top straight up and away from the auto-injector.
- Your EpiPen auto-injector may come in a package with a gray trainer and separate Trainer Instructions for Use. The gray trainer contains no medicine and no needle. Keep the trainer and the real EpiPen auto-injectors away from young children. The real EpiPen auto-injectors and trainer are not toys. For young children, use of the trainer and the real EpiPen auto-injectors should be supervised by an adult. Regularly practice with your gray trainer in non-emergency situations to make sure you can safely use the real EpiPen auto-injector in an emergency. Always carry your 2 real EpiPen auto-injectors with you in case of an allergic emergency. Additional training information is available at www.epipen.com.
- Do not drop the protective case, EpiPen auto-injector or auto-injector. If the protective case or auto-injector is dropped, check for damage and leakage. If damage or leakage is noticed or suspected, throw away (dispose of) the EpiPen auto-injector and protective case and replace it.

What are the possible side effects of EpiPen ?

EpiPen may cause serious side effects.

- EpiPen should only be injected into the middle of your outer thigh (upper leg). Do not inject EpiPen into your:oveinsobuttocksofingers, toes, hands or feet

If you accidentally inject EpiPen into any place other than the middle of your outer thigh, go to the nearest emergency room right away. Tell the healthcare provider where on your body you received the accidental injection.

- Rarely, people who have used the EpiPen auto-injector may get infections at the injection site within a few days of an injection. Some of these infections can be serious. Call your healthcare provider right away if you see any of the following at an injection site:oredness that does not go awayoswellingotendernessothe area feels warm to the touch
- Cuts on the skin, bent needles and needles that remain in the skin after the injection can happen when young children kick or move during an injection. If you inject a young child with an EpiPen auto-injector, hold their leg firmly in place before and during the 3 second injection to prevent injuries. Follow the Instructions for Use at the end of this Patient Information leaflet. Ask your healthcare provider to show you how to:

1. Hold the young child firmly in place (restrain).

2. With one hand, grip the auto-injector with the orange needle end pointing down.

3. With the other hand, pull the blue safety top straight up and away from the auto-injector.

- If you have certain medical conditions, or take certain medicines, your condition may get worse or you may have longer lasting side effects when you use your EpiPen auto-injector. Talk to your healthcare provider about all your medical conditions.

Common side effects of EpiPen include:

- fast, irregular or “pounding” heartbeat
- sweating
- headache
- weakness
- shakiness
- paleness
- feelings of over excitement, nervousness or anxiety
- dizziness
- nausea or vomiting
- breathing problems

These side effects may go away with rest. Tell your healthcare provider if you have any side effect that bothers you or that does not go away.

These are not all the possible side effects of EpiPen . For more information, ask your healthcare provider or pharmacist.

Call your doctor for medical advice about side effects. You may report side effects to FDA at 1-800-FDA-1088.

How should I store EpiPen auto-injectors?

- Store EpiPen auto-injectors at room temperature between 68° F to 77° F (20° C to 25° C).
- Keep this medicine out of the sight and reach of young children.
- Keep protective case in the outer carton to protect from light. When exposed to air or light epinephrine changes quickly to a pinkish or brown color and should not be used.
- Do not expose to extreme cold or heat. For example, do not store in your vehicle’s glove box or trunk. Do not store in the refrigerator or freezer.
- Examine the contents in the medicine viewing window of your EpiPen auto-injector regularly. The medicine should be clear. If the medicine is discolored (pinkish or brown color) or contains solid particles, replace the auto-injector.
- Always keep your 2 EpiPen auto-injectors in the protective cases to prevent damage to the device. The protective case is not waterproof.
- The blue safety top helps to prevent accidental injection. Keep the blue safety top in place until you need to use the EpiPen auto-injector. After the auto-injector is used, throw away the blue safety top as this may pose a choking hazard for small children.

Disposing of an Expired, Unused or Used EpiPen Auto-Injector

Your EpiPen auto-injector has an expiration date. Replace the pack of auto-injectors before the expiration date. Throw away (dispose of) expired, unwanted, or unused EpiPen auto-injectors in an FDA-cleared sharps disposal container right away after use. Do not throw away the EpiPen in your household trash. If you do not have an FDA-cleared sharps disposal container, you may use a household container that is:

- Made of heavy-duty plastic,
- Can be closed with a tight-fitting, puncture-resistant lid, without sharps being able to come out,
- Upright and stable during use,
- Leak-resistant, and
- Properly labeled to warn of hazardous waste inside the container.

When your sharps disposal container is almost full, you will need to follow your community guidelines for the right way to dispose of your sharps disposal container. There may be state or local laws about how you should throw away used needles and syringes. For more information about safe sharps disposal, and for specific information about sharps disposal in the state that you live in, go to the FDA’s website at: http://www.fda.gov/safesharpsdisposal

Visit the FDA’s website (https://www.fda.gov/drugs/safe-disposal-medicines/disposal-unused-medicines-what-you-should-know) for more information about how to throw away unused, unwanted or expired medicines.

After using your EpiPen auto-injector in an allergic emergency, get emergency medical help right away. Take your used EpiPen auto-injector with you to give to your healthcare provider for disposal.

General information about the safe and effective use of EpiPen auto-injectors.

Medicines are sometimes prescribed for purposes other than those listed in a Patient Information leaflet. Do not use the EpiPen auto-injector for a condition for which it was not prescribed. Do not give your EpiPen auto-injector to other people.

This Patient Information leaflet summarizes the most important information about the EpiPen auto-injectors. If you would like more information, talk to your healthcare provider. You can ask your pharmacist or healthcare provider for information about EpiPen auto-injectors that is written for health professionals.

What are the ingredients in EpiPen ?

Active Ingredients: epinephrine

Inactive Ingredients: sodium chloride, sodium metabisulfite, hydrochloric acid, and water

Important Information

- The EpiPen auto-injector has a yellow colored label.
- Your EpiPen auto-injector is designed to work through clothing.
- When receiving an EpiPen auto-injector and before you need to use the EpiPen auto-injector, remove the auto-injector from the protective case and check the auto-injector to make sure the blue safety top is not raised (see Figure Din the Instructions for Use). If the blue safety top is raised, the auto-injector should notbe used because the device could activate by accident. Do nottry to push the blue safety top back down. Put the auto-injector back in the protective case and replace it with a new EpiPen.
- Choking hazard: The blue safety top is a small part that may become a choking hazard for children. Throw away the blue safety top immediately after using the EpiPen auto-injector.
- It is very important that you hold the EpiPen auto-injector down firmly on the middle of the outer thigh (upper leg) for at least 3 full seconds. If you do not hold it in place long enough, the EpiPen auto-injector might not deliver the correct dose of medicine.
- If an accidental injection happens, get emergency medical help right away.
- Do not place patient information or any other foreign objects in the protective case with the EpiPen auto-injector, as this may prevent you from removing the auto-injector for use.
- Each EpiPen auto-injector can be used only 1 time (single-use). The auto-injectors deliver a fixed dose of epinephrine and cannot be reused. Do not try to reuse EpiPen after the device has been activated. It is normal for most of the medicine to remain in the auto-injector after the dose is injected. The correct dose has been administered if the orange needle end is extended to cover the needle and the medicine viewing window is blocked.
- Incorrect Use and Correct Use of EpiPen

Incorrect Use | Correct Use and; Important Reminders
Storage outside the protective case or storage of the EpiPen auto-injector in extreme cold or heat. | Always keep your EpiPen stored in the protective case and at room temperature. Keep protective case in the outer carton to protect from light. Wrong storage may stop the EpiPen from working. If the device has been in extreme cold or heat, the EpiPen should be replaced.
Failing to remove the auto-injector from the protective case before use. | The EpiPen auto-injector must be removed from the protective case it comes in before use.
Failing to remove the blue safety top before use. | Remove the blue safety top before use. EpiPen will not activate with the blue safety top in place.
Activating the auto-injector upside down which will cause an injection into the hand. | The needle exits from the orange end of the EpiPen auto-injector, which should be in contact with the outer thigh (upper leg) at a 90˚angle (perpendicular) to the thigh before and during activation. The orange needle end will extend to cover the needle after activation. If you can still see the needle, do not try to reuse the auto-injector.
Failing to apply enough force to activate the EpiPen auto-injector. | EpiPen should be administered by swinging and pushing the auto-injector firmly against the outer thigh. EpiPen auto-injectors make a distinct pop sound when pushed against the thigh. The pop sound signals that the injection has started. The correct dose has been administered if the orange needle end is extended and the window is blocked.
Administering at an injection site other than the outer thigh. | Administer EpiPen in the outer thigh only.
Failing to hold the auto-injector in place for a full 3 seconds. | Hold the EpiPen auto-injector in place for a full 3 seconds following activation (count slowly 1, 2, 3).

For more information and video instructions on the use of EpiPen auto-injectors, go to www.epipen.comor call 1-800-395-3376.

INSTRUCTIONS FOR USE

EPIPEN® [/epeepen/]
(epinephrine injection, USP) Auto-Injector 0.3 mg
EpiPen®= one dose of 0.3 mg epinephrine,
USP 0.3 mg/0.3 mL
for intramuscular and subcutaneous use

This Instructions for Use contains information on how to administer the EpiPen auto-injector.

Figure A. Single 0.3 mg dose, EpiPen auto-injector (with yellow label)

Important Information You Need to Know Before Administering the EpiPen Auto-Injector

- The single-dose EpiPen auto-injector is for allergic emergency (anaphylaxis) and should be used right away. You can use a second EpiPen auto-injector if symptoms continue or symptoms come back.
- Before you need to use your EpiPen auto-injector, make sure your healthcare provider shows you the right way to use it. Anyone who may be able to administer the EpiPen auto-injector should also understand how to use it.
- Carefully read the Instructions for Use in a non-emergency situation and make sure you understand them before using your EpiPen auto-injector.
- If you have any questions, ask your healthcare provider.
- It is very important that you hold the EpiPen auto-injector down for at least 3 full seconds. If you do not hold it in place long enough, the EpiPen auto-injector might not have time to deliver the correct dose of medicine.
- Make sure to always carry 2 EpiPen auto-injectors. One dose may not be enough.
- Inject EpiPen into the muscle (intramuscular) or under the skin (subcutaneous) in the middle of the outer thigh (see Figure B). Do not inject EpiPen into any other part of the body.
- The injection can be given through clothes.

Figure B. Inject into middle of the outer thigh

- Each EpiPen auto-injector can be used only 1 time (single-use). It is normal for most of the medicine to remain in the auto-injector after the dose is injected. The correct dose has been administered if the orange needle end is extended to cover the needle and the medicine viewing window is blocked.

- Warning: Do notflip the blue safety top off using a thumb or by pulling it sideways, or by bending and twisting the blue safety top. This may cause the device to activate by accident: a “pop” is heard, the orange needle end is extended and the medicine viewing window is blocked. A device that has been activated by accident cannot be used in an emergency. If this happens, replace it with a new EpiPen .
- Do not take the EpiPen auto-injector apart.
- Keep the blue safety top in place until you are ready to inject.
- Always point the orange needle end down (see Figure C). Keep your fingers, thumb and hand away from the orange needle end. Accidental injection in the fingers, thumb or feet may cause loss of blood flow to these areas.

Figure C. Correct way to hold the EpiPen auto-injector with orange needle end pointing down

Checking the Blue Safety Top

When receiving an EpiPen auto-injector and before you need to use the EpiPen auto-injector, do the following:

- Remove the EpiPen auto-injector from the protective case and check the auto-injector to make sure the blue safety top is not raised (see Figure D). If the blue safety top is not raised, the auto-injector is okay to use. Put the auto-injector back in the protective case so that it is ready to be used in an allergic emergency.
- If the blue safety top is raised(see Figure E) , the auto-injector should not be usedbecause the device could activate by accident. Do nottry to push the blue safety top back down. Put the auto-injector back in the protective case and replace it with a new EpiPen .

Preparing to Inject EpiPen

Note the following while preparing to inject EpiPen :

- Remove anything in or around the injection site that blocks you from giving the injection.
- Check the auto-injector before use. If the auto-injector appears damaged, throw it away (dispose of) and do not use.
- The gray trainer contains no medicine and no needle. Practice with the gray trainer before an allergic emergency happens to make sure you can safely use the real EpiPen in an emergency.

Figure F. Gray Trainer

- Keep the trainer and the real EpiPen auto-injectors away from young children. The EpiPen auto-injectors and trainer are not toys. Use by young children should be supervised by an adult.

- While preparing to inject, make sure you know where to inject (see Figure B) and how to hold the EpiPen auto-injector (see Figure C).
- EpiPen auto-injectors have a Never-See-Needle®that covers the needle before and after you inject (see Figure G). You should never see a needle. If you can see a needle, do not use the EpiPen auto-injector.

Figure G. Never-See-Needle

Figure G. Never-See-Needle

Make sure the EpiPen auto-injector has notbeen used. If an EpiPen auto-injector has been used:

- the orange needle end will be extended (see Step 4),
- the medicine viewing window will be blocked, and
- the EpiPen auto-injector will no longer fit in the protective case.

Preparing to Inject a Child

- If you are giving EpiPen to a young child, first hold the child firmly in place (restrain) and then use both hands to remove the blue safety top as shown (see Figure J). Use one hand to hold the auto-injector with the orange needle end pointing down and your other hand to remove the blue safety top to activate the auto-injector. Then, inject in the middle of the outer thigh (see Figure L). Remember to hold the leg firmly in place before and during the 3 second injection to avoid needlestick injuries including cuts to the thigh.
- Keep the trainer and the real EpiPen auto-injectors away from young children. The real EpiPen auto-injectors and trainer are not toys. Use by young children should be supervised by an adult.

Checking the Medicine Color

Examine the liquid in the medicine viewing window of your EpiPen auto-injector regularly. See the information below:

Medicine Color:

- The medicine can be seen through the medicine viewing window located near the middle of the EpiPen auto-injector.

To check the medicine color, hold the auto-injector in front of a white background in a well-lit area and look through the medicine viewing window.

Figure H. Medicine Viewing Window

✓Use the medicine if it is clear and colorless.

Do not use the medicine if it is discolored (pinkish or brown color) or if the medicine has particles floating in it. Throw it away (dispose of) and use a new EpiPen auto-injector (see the section “ Disposing of an Expired, Unused or Used EpiPen Auto-Injector” on the Patient Information side of this leaflet).

Injecting EpiPen

Step 1 Slide the EpiPen auto-injector out of the case (Figure I)

Remove the auto-injector from the protective case.

Figure I.

Step 2 Pull off the blue safety top (Figure J)

Grip the EpiPen auto-injector with one hand and with the orange needle end pointing down. Use the other hand to remove the blue safety top. Pull it straight up and away .

Figure J.

Note:Do not twist or bend the blue safety top. Failure to pull out the blue safety top correctly (straight up and away) can cause accidental activation.

Note:To avoid an accidental injection, never put your thumb, fingers or hand over the orange needle end. If an accidental injection happens, get emergency medical help right away.

Step 3 Inject the medicine by self (Figure K) or caregiver (Figure L) administration

Place the orange needle end against the outer thigh, through clothing if needed.

Push down firmly and hold in place for 3 seconds.

Note:EpiPen auto-injectors make a distinct pop sound when pushed against the thigh. This is normal and means that the EpiPen auto-injector is working. After the pop, continue to press the EpiPen auto-injector down firmly on the outer thigh for 3 seconds to make sure that the medicine is given.

Figure K.

Figure L.

Step 4 Check if used (Figure M)

Lift the auto-injector straight out from the thigh.

The orange needle end will extend to cover the needle. If the needle is visible, do not reuse it. Use a new auto-injector.

Throw away the blue safety top.

Figure M.

Step 5 Get emergency medical help

After injecting EpiPen , get emergency medical help right away. You can use a second EpiPen auto-injector if symptoms continue or come back.

- Take your used EpiPen auto-injector to your healthcare provider.
- EpiPen are single-dose auto-injectors and cannot be reused.
- If the needle is visible, do not try to reuse it.

Storing EpiPen Auto-Injectors

Store the EpiPen auto-injectors at room temperature between 68˚ F to 77˚ F (20˚ C to 25˚ C).

Keep protective case in the outer carton to protect from light. When exposed to air or light, the medicine in the EpiPen auto-injector changes rapidly to a pinkish or brown color and should not be used.

Disposing of EpiPen Auto-Injectors

After using your EpiPen auto-injector, get emergency medical help right away. Take your used auto-injector with you to give to your healthcare provider for disposal.

Important:The blue safety top is a small part that may become a choking hazard for children. Throw away the blue safety top immediately after using the EpiPen auto-injector.

Your EpiPen auto-injector has an expiration date. Replace it before the expiration date.

For more information on how to throw away (dispose of) your expired EpiPen auto-injector, see the section “ Disposing of an Expired, Unused or Used EpiPen Auto-Injector” on the Patient Information side of this leaflet.

Relabeled by:

Enovachem PHARMACEUTICALS

Torrance, CA 90501

EPIPEN®
(epinephrine injection, USP) Auto-Injector 0.3 mg
EpiPen®= one dose of 0.3 mg epinephrine, USP 0.3 mg/0.3 mL

For more information about EpiPen auto-injectors and proper use of the product, call Mylan at 1-877-446-3679 or visit www.epipen.comfor an instructional video.

EpiPen Trainer Instructions for Use

In an emergency: Do not use the gray Trainer. Use your real yellow EpiPen® auto-injector.

Important Information

- The Trainer label has a gray color.
- The Trainer contains no medicine and no needle.The orange end of the Trainer is the needle end of the real yellow EpiPen auto-injector.
- Regularly practice with the gray Trainer in non-emergency situations to make sure you are able to safely use the real yellow EpiPen auto-injector in an emergency situation.
- Always carry your 2 real yellow EpiPen auto-injectors in case of an allergic emergency.
- In an actual emergency, you need to use your real yellow EpiPen auto-injector immediately. You should get emergency medical help right away after using your real yellow EpiPen auto-injector.
- When receiving the real yellow EpiPen auto-injector and before you need to use the real yellow EpiPen auto-injector, check the auto-injector to make sure the blue safety top is not raised (see Patient Information leaflet). If the blue safety top is raised, the auto-injector should not be usedbecause the device could activate by accident. Do nottry to push the blue safety top back down. Put the auto-injector back in the protective case and replace it with a new real yellow EpiPen.
- Choking hazard:The blue safety top is a small part that may become a choking hazard for children. Put the blue safety top back on the Trainer and reset it immediately after practicing.
- Keep the gray Trainer away from young children. The Trainer is not a toy. Children should only practice with the Trainer under adult supervision.
- Carefully read the Instructions for Use for the real yellow EpiPen auto-injector in a non-emergency situation and make sure you understand them before using the real yellow EpiPen .

The EpiPen Trainer

Familiarize yourself with this gray Trainer. Practice until you are comfortable using it.

Your gray Trainer:

Figure A. Your Gray Trainer

Figure A. Your Gray Trainer

Caution: Know the difference between the Trainer and your real yellow EpiPen Auto-Injector

Important differences between the Trainer and your real yellow EpiPen auto-injector

 | Trainer (Gray) | EpiPen (Yellow)
Contains medicine? | No | Yes
Has needle? | No | Yes
Comes in Protective Case? | No | Yes
Color of Label? | Gray | Yellow
Has expiration date? | No | Yes
Can be reused? | Yes | No(use only one time)
Okay to remove and replace blue safety top? | Yes | No(remove just one time before use)
Pressure needed to hold against thigh? | Moderate | Strong

Practice Instructions

Using the Trainer

Step 1 Pull off the blue safety top (Figure B)

Grip the gray Trainer with one hand and with the orange end pointing down. Use the other hand to remove the blue safety top. Pull it straight up and away. Note:Do not twist or bend the blue safety top.

Warning: Do notflip the blue safety top off using a thumb or by pulling it sideways or by bending and twisting the blue safety top. This may cause the real yellow EpiPen auto-injector to accidentally activate. An EpiPen auto-injector that has been activated by accident cannot be used for a patient in an emergency and must be replaced.

Figure B

Step 2 Trainer injection simulation by self (Figure C) or caregiver (Figure D) administration

Place the orange end against the outer thigh, over clothing if needed.

Push down firmly and hold in place for 3 seconds. If practicing an injection on a young child, first hold the child firmly (restrain) and then use one hand to hold the Trainer with the orange end pointing down and your other hand to remove the blue safety top. Hold the leg firmly in place before and during the 3 second practice injection to prevent injuries.

Note:The Trainer makes a distinct pop sound when pushed against the thigh. This is normal and means that the auto-injector is working. After the pop, continue to press the Trainer down firmly on the outer thigh for 3 seconds.

Figure C

Figure D

Step 3 Check if used (Figure E)

Lift the Trainer straight out from the thigh. Inspect: The Trainer was activated correctly if the orange end is extended. If the orange end is not extended, repeat Step 1 and Step 2.

Figure E

Step 4 Reset the Trainer (Figure F)

Put the blue safety top back on the Trainer immediately. Place the orange end on a hard surface. Squeeze the sides of the orange end and push down on the Trainer with the other hand. Note:This resetting step should never be used with a real yellow EpiPen auto-injector as this may result in injury.

Never put your thumb, other fingers, or hand over the orange (needle) end of the real yellow EpiPen auto-injector.

Figure F

Practice Session Information

In case of an allergic emergency, use the real yellow EpiPen auto-injector and not the gray Trainer.

Follow instructions above. Repeat as often as needed until you are able to inject quickly and correctly. Regularly practice with the Trainer to make sure that you are able to use the real yellow EpiPen auto-injector in an emergency situation.

Reread:

- The Trainer Instructions for Use
- The “Patient Information” leaflet that comes with your EpiPen auto-injector

Train others who could help you in an emergency:

- Anyone who may be able to administer the EpiPen auto-injector should know how to help you during an allergic emergency. Before an emergency occurs, have them:
- Regularly practice preparing the Trainer for injection and simulating an injection
- Read the Trainer Instructions for Use and the “Patient Information” leaflet

For more information about the EpiPen auto-injector and the proper use of the products, go to www.epipen.com.

Relabeled by:

Enovachem PHARMACEUTICALS

Torrance, CA 90501